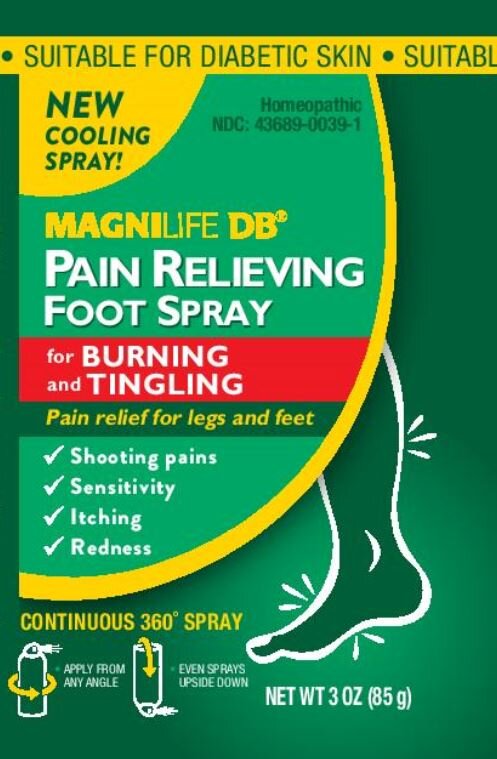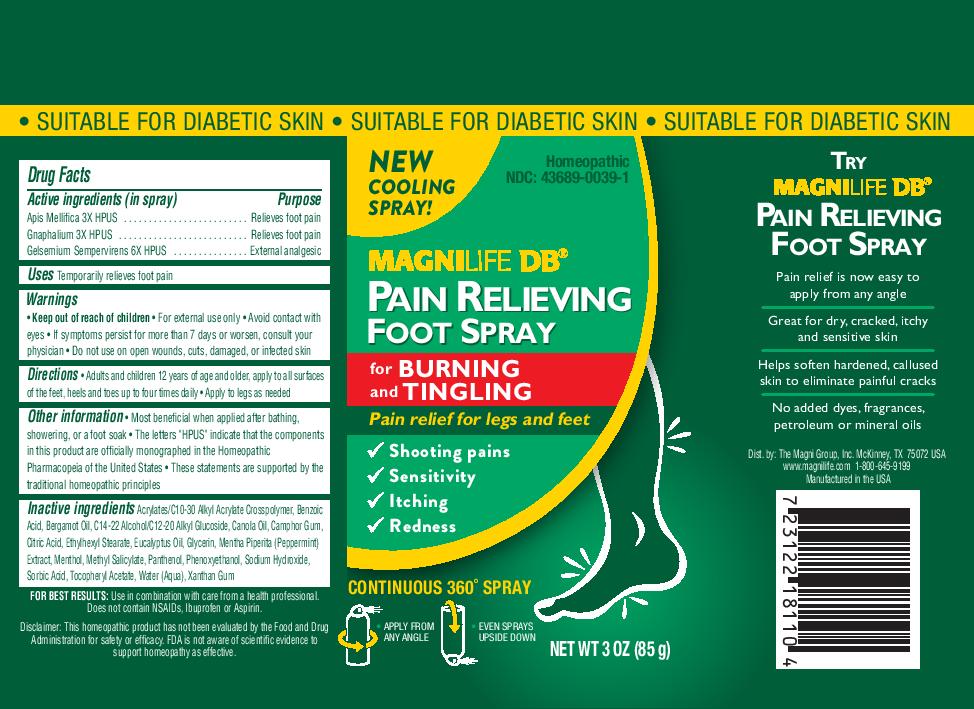 DRUG LABEL: DB Foot Pain Relieving
NDC: 43689-0039 | Form: SPRAY
Manufacturer: The Magni Group Inc
Category: homeopathic | Type: HUMAN OTC DRUG LABEL
Date: 20201229

ACTIVE INGREDIENTS: PSEUDOGNAPHALIUM LUTEOALBUM LEAF 3 [hp_X]/100 g; APIS MELLIFERA 3 [hp_X]/100 g; GELSEMIUM SEMPERVIRENS ROOT 6 [hp_X]/100 g
INACTIVE INGREDIENTS: WATER; C12-20 ALKYL GLUCOSIDE; CANOLA OIL; ETHYLHEXYL STEARATE; METHYL SALICYLATE; SORBIC ACID; MENTHOL; CAMPHOR (SYNTHETIC); PANTHENOL; .ALPHA.-TOCOPHEROL ACETATE; C14-22 ALCOHOLS; MENTHA X PIPERITA WHOLE; BERGAMOT OIL; GLYCERIN; EUCALYPTUS OIL; XANTHAN GUM; CARBOMER COPOLYMER TYPE B (ALLYL PENTAERYTHRITOL CROSSLINKED); SODIUM HYDROXIDE; CITRIC ACID MONOHYDRATE; BENZOIC ACID; PHENOXYETHANOL

Active Ingredients (In Spray) - Purpose Apis Mellifica 3X HPUS - Relieves Foot Pain Gnaphalium 3X HPUS - Relieves Foot Pain Gelsemium Sempervirens 6X HPUS - External Analgesic

NDC: 43689-0039

Purpose: Relieves Foot Pain External Analgesic

NDC: 43689-0039

Use: Temporarily Relieves Foot Pain

NDC: 43689-0039

Keep out of reach of children

NDC: 43689-0039

Warnings: For external use only

NDC: 43689-0039

When using this product: - Avoid contact with eyes

NDC: 43689-0039

If symptoms persist for more than 7 days or worsen, consult your physician

NDC: 43689-0039

Do not use on open wounds, cuts, damaged, or infected skin

NDC: 43689-0039

Directions: - Adults and children 12 years of age and older, apply to all surfaces on the feet, heels and toes up to four times daily - Apply to legs as needed

NDC: 43689-0039

Other information: - Most beneficial when applied after bathing, showering, or a foot soak - The letters "HPUS" indicate that the components in this product are officially monographed in the Homeopathic Pharmacopeia of the United States - These statements are supported by the traditional homeopathic principles

NDC: 43689-0039

Inactive Ingredients: Acrylates/C10-30 Alkyl Acrylate Crosspolymer, Benzoic Acid, Bergamot Oil, C14-22 Alcohol/C12-20 Alkyl Glucoside, Canola Oil, Camphor Gum, Citric Acid, Ethylhexyl Stearate, Eucalyptus Oil, Glycerin, Mentha Piperita (Peppermint) Extract, Menthol, Methyl Salicylate, Panthenol, Phenoxyethanol, Sodium Hydroxide, Sorbic Acid, Tocopheryl Acetate, Water (Aqua), Xanthan Gum

NDC: 43689-0039

Principal Display Panel

NDC: 43689-0039